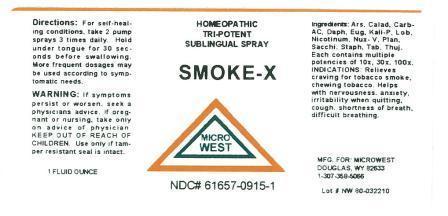 DRUG LABEL: SMOKE-X
NDC: 61657-0915 | Form: LIQUID
Manufacturer: White Manufacturing Inc. DBA Micro-West
Category: homeopathic | Type: HUMAN OTC DRUG LABEL
Date: 20121206

ACTIVE INGREDIENTS: ARSENIC TRIOXIDE 10 [hp_X]/30 mL; DIEFFENBACHIA SEGUINE 10 [hp_X]/30 mL; PHENOL 10 [hp_X]/30 mL; DAPHNE ODORA BARK 10 [hp_X]/30 mL; SYZYGIUM JAMBOS SEED 10 [hp_X]/30 mL; POTASSIUM PHOSPHATE, DIBASIC 10 [hp_X]/30 mL; LOBELIA INFLATA 10 [hp_X]/30 mL; NICOTINE 10 [hp_X]/30 mL; STRYCHNOS NUX-VOMICA SEED 10 [hp_X]/30 mL; PLANTAGO MAJOR 10 [hp_X]/30 mL; SUCROSE 10 [hp_X]/30 mL; DELPHINIUM STAPHISAGRIA SEED 10 [hp_X]/30 mL; TOBACCO LEAF 10 [hp_X]/30 mL; THUJA OCCIDENTALIS LEAF 10 [hp_X]/30 mL
INACTIVE INGREDIENTS: POTASSIUM SORBATE

DRUG FACTS

ACTIVE INGREDIENT

EACH MULTIPLE CONCENTRATES OF 10X, 30X, 100X
ARSENICUM ALBUM [HPUS]
CALADIUM SEGUINUM [HPUS)
CARBOLICUM ACIDUM [HPUS]
DAPHNE INDICA [HPUS]
EUGENIA JAMBOSA [HPUS]
KALI PHOSPHORICUM [HPUS]
LOBELIA INFLATIA
NICOTINUM [HPUS]
NUX VOMICA [HPUS]
PLANTAGO MAJOR [HPUS]
SACCHARUM OFFICINALE [HPUS]
STAPHYSAGRIA [HPUS]
TABACUM [HPUS]
THUJA OCCIDENTALIS

PURPOSE

RELIEVES CRAVING FOR TOBACCO SMOKE, CHEWING TOBACCO. HELPS WITH NERVOUSNESS, ANXIETY, IRRITABILITY WHEN QUITTING, COUGH, SHORTNESS OF BREATH, DIFFICULT BREATHING

KEEP OUT OF REACH OF CHILDREN

INDICATIONS AND USAGE

INDICATIONS: RELIEVES CRAVING FOR TOBACCO SMOKE, CHEWING TOBACCO. HELPS WITH NERVOUSNESS, ANXIETY, IRRITABILITY WHEN QUITTING, COUGH, SHORTNESS OF BREATH, DIFFICULT BREATHING

WARNINGS

WARNING: IF SYMPTOMS PERSIST OR WORSEN, SEEK A PHYSICIANS ADVICE. IF PREGNANT OR NURSING, TAKE ONLY ON ADVICE OF PHYSICIAN. USE ONLY IF TAMPER RESISTANT SEAL IS IN TACT

DIRECTIONS

DIRECTIONS: FOR SELF-HEALING CONDITIONS, TAKE 2 PUMP SPRAYS 3 TIMES DAILY. HOLD UNDER TONGUE 30 SECONDS BEFORE SWALLOWING. MORE FREQUENT DOSAGES MAY BE USED ACCORDING TO SYMPTOMATIC NEEDS

INACTIVE INGREDIENT

POTASSIUM SORBATE AS STABILIZER

MANUFACTURE

MANUFACTURED FOR MICRO-WEST

DOUGLAS, WY 82633

1-307-358-5066